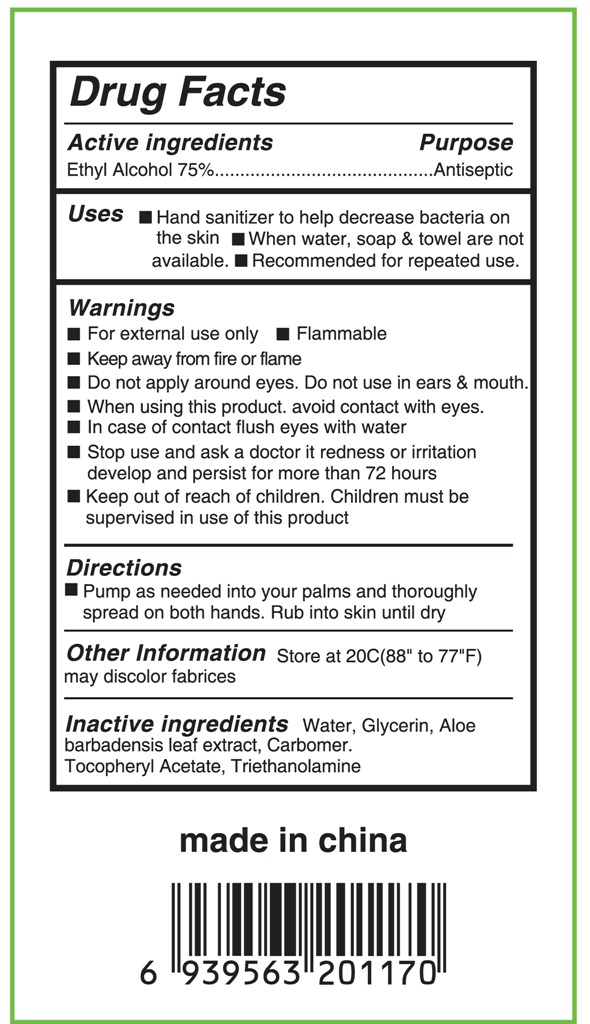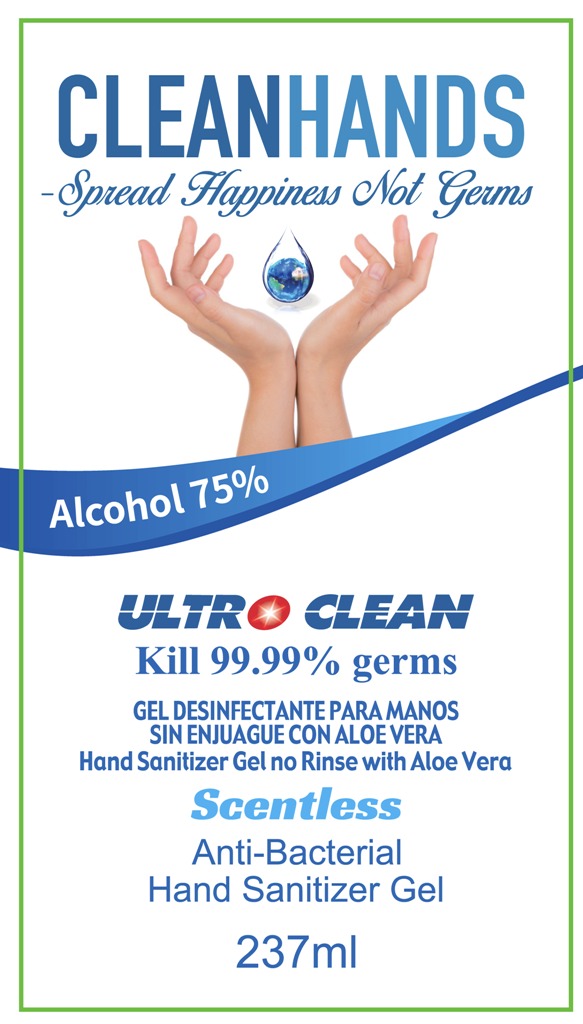 DRUG LABEL: hand sanitizer
NDC: 73788-002 | Form: GEL
Manufacturer: Hangzhou Huiji Biotechnology Co., Ltd.
Category: otc | Type: HUMAN OTC DRUG LABEL
Date: 20220224

ACTIVE INGREDIENTS: ALCOHOL 75 mL/100 mL
INACTIVE INGREDIENTS: WATER; GLYCERIN; ALOE VERA LEAF; TROLAMINE; CARBOMER 934; .ALPHA.-TOCOPHEROL ACETATE

73788-002 hand sanitizer 75% Ethyl Alcohol

Active Ingredient

Ethyl Alcohol 75%

Purpose

Antiseptic

Use

■ Hand sanitizer to help decrease bacteria on
the skin
■When water, soap & towel are not
available.
■Recommended for repeated use,

WARNINGS

For external use only■ Flammable
Keep away from fire or flame
Do not apply around eyes. Do not use in ears & mouth.
When using this product. avoid contact with eyes.
In case of contact flush eyes with water
Stop use and ask a doctor it redness or irritation
develop and persist for more than 72 hours

Keep out of reach of children. Children must be
supervised in use of this product

Directions

Pump as needed into your palms and thoroughly
spread on both hands. Rub into skin until dry
Other Information Store at 20C(88" to 77"F)
may discolor fabrices

Inactive ingredients

Water, Glycerin, Aloe
barbadensis leaf extract, Carbomer.
Tocopheryl Acetate, Triethanolamine